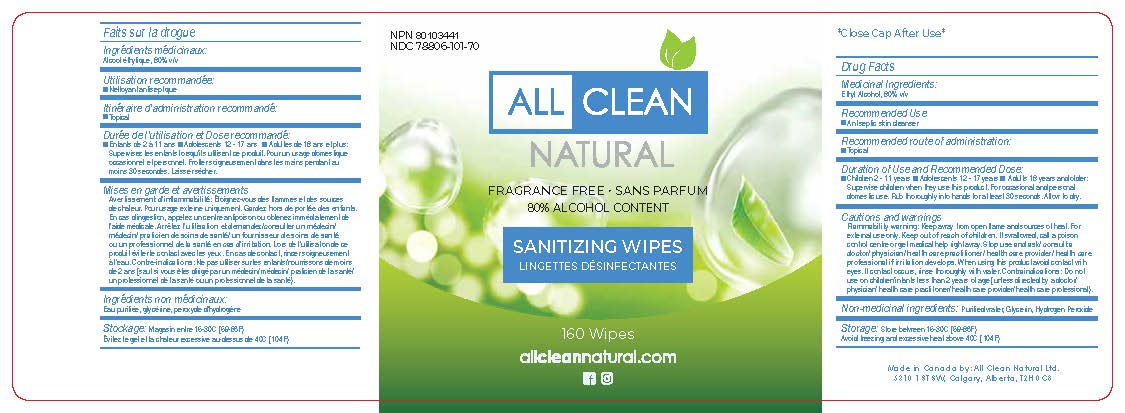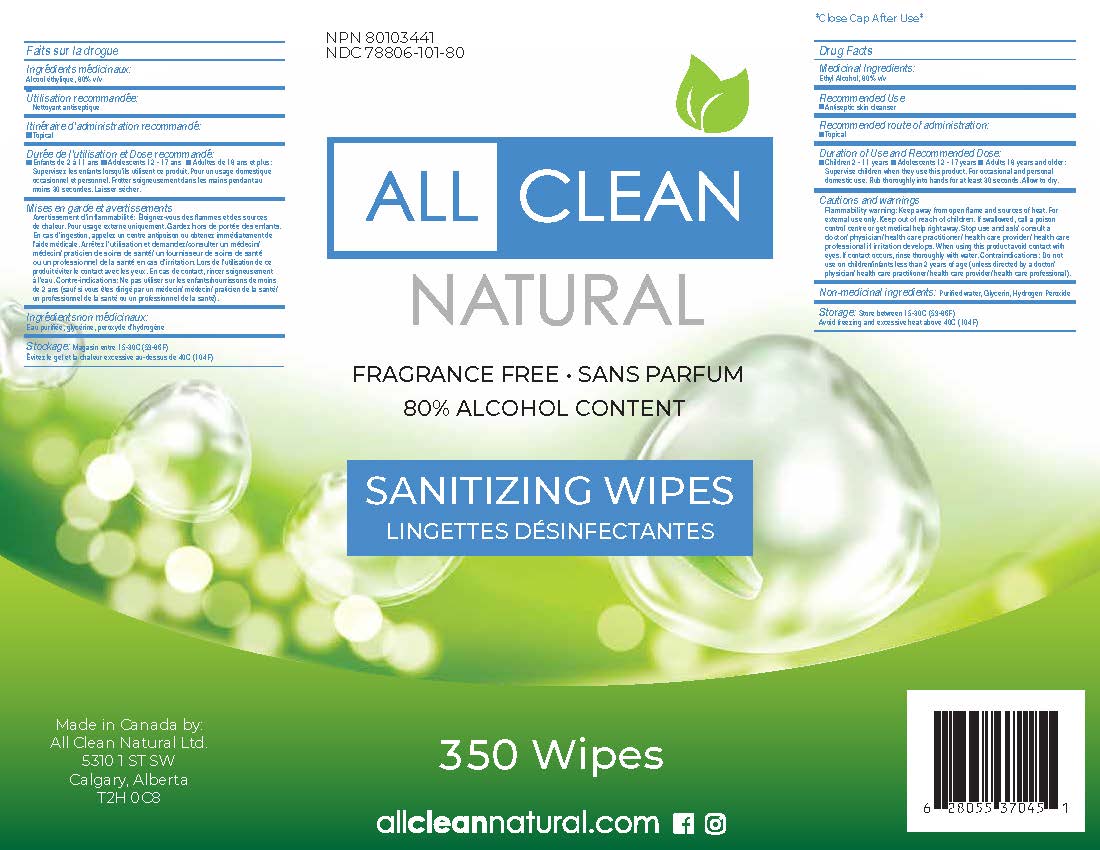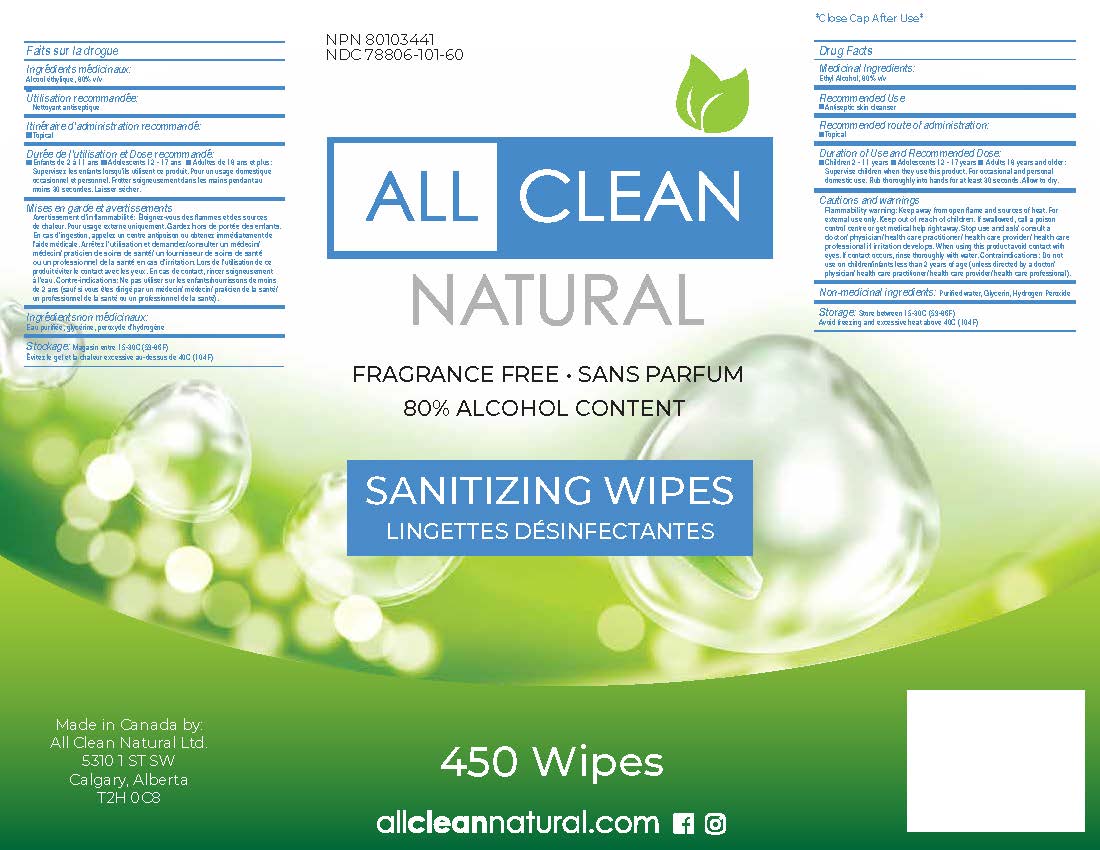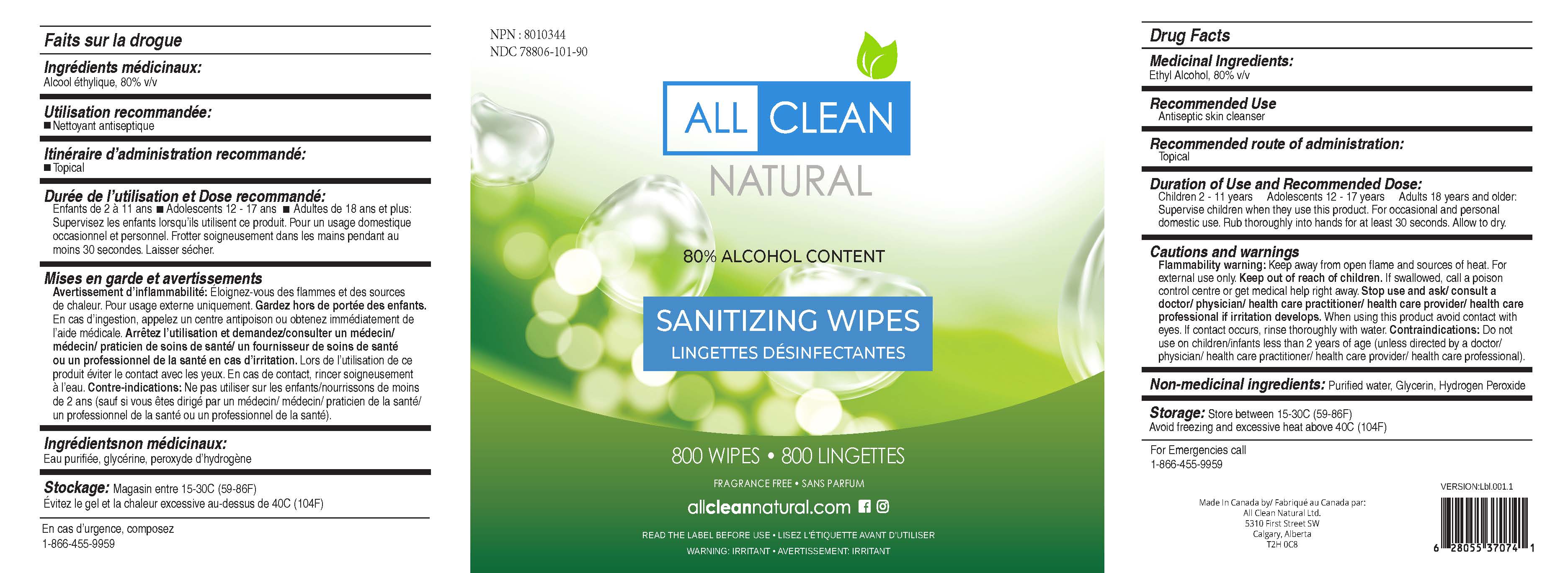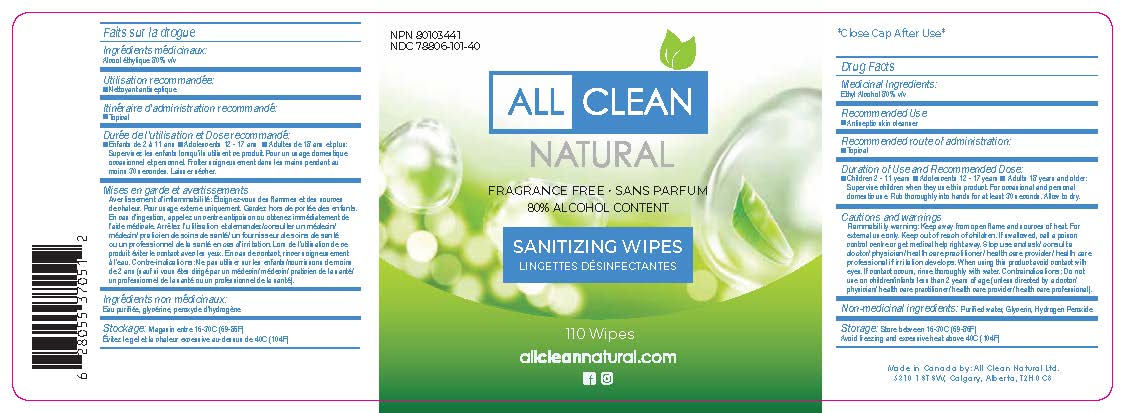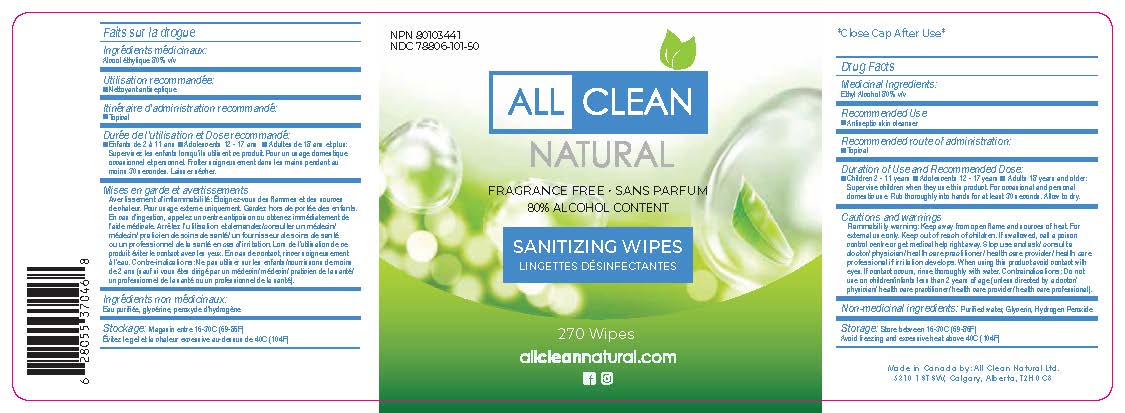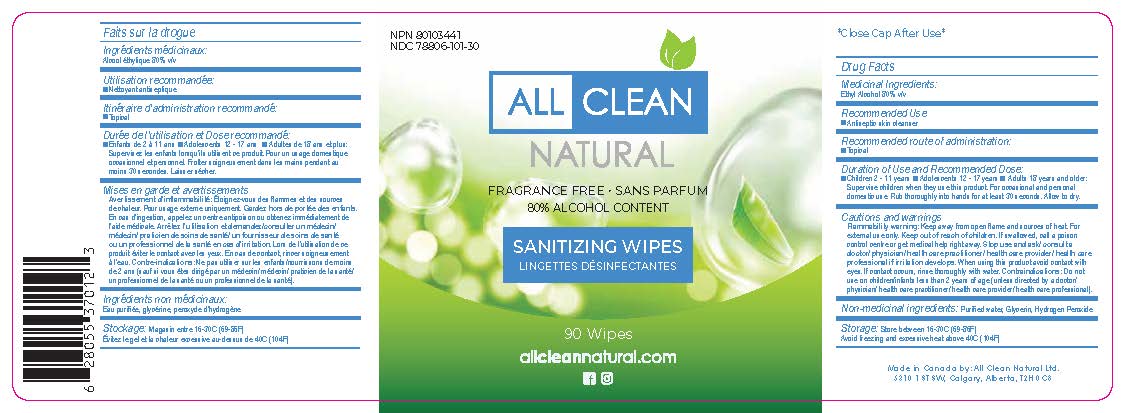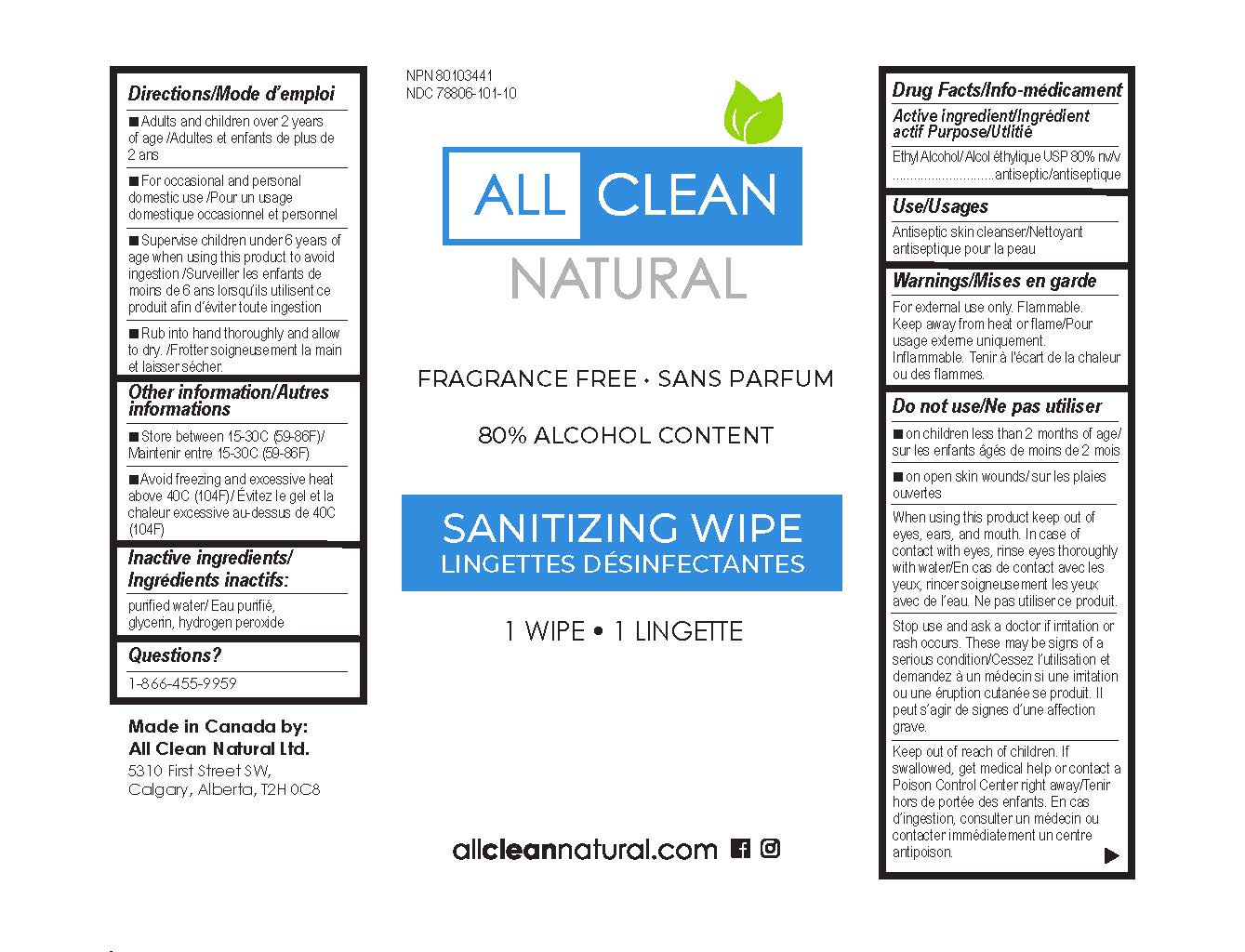 DRUG LABEL: All Clean Natural Sanitizer Wipes
NDC: 78806-101 | Form: CLOTH
Manufacturer: All Clean Natural Ltd
Category: otc | Type: HUMAN OTC DRUG LABEL
Date: 20210428

ACTIVE INGREDIENTS: ALCOHOL 80 mL/100 mL
INACTIVE INGREDIENTS: WATER; GLYCERIN; HYDROGEN PEROXIDE

All Clean Natural Sanitizer Wipes

Active ingredient

Ethyl Alcohol/ Alcool éthylique USP 80% v/v

Purpose

Antiseptic

Use

Antiseptic skin cleanser/Nettoyant antiseptique pour la peau

Warnings

For external use only. Flammable. Keep away from heat or flame.

Do Not Use

- On children less than 2 months of age

- On open skin wounds

Stop use and ask a doctor if irritation or rash occurs. These may be signs of a serious condition.

When using this product keep out of eyes, ears, and mouth. In case of contact with eyes, rinse eyes thoroughly with water.

keep out of reach of children.

If swallowed, get medical help or contact a Poison Control Center right away.

Directions

Place enough product on hands to cover all surfaces. Rub hands together until dry. Supervise children under 6 years of age when using this product to avoid swallowing.

Other Information

- Store between 15-30C (59-86F)

- Avoid freezing and excessive heat above 40C (104F)

Inactive ingredients

Purified water, Glycerin, Hydrogen Peroxide

FRAGRANCE FREE

*Close Cap After Use*

NPN 80103441
NDC 78806-101-50

Manufactured By:
All Clean Natural
5310 1 St SW
Calgary, AB T2H 0C8

allcleannatural.com

DIRECTIONS: For first use, remove lid. Thread wipe from center of roll through dispensing hole in the lid and pull wipe up and slightly downwards to the side. Snap lid securely shut. Remove cap and pull wipe to the side to dispense. Keep cap closed between uses to prevent moisture loss. Wipe hands, discard.

WARNING: For external use only. Do not ingest. If ingested, drink plenty of water and contact poison control. Avoid contact with eyes. If contact occurs, flush thoroughly with water. If skin irritation occurs, discontinue use. Keep out of reach of children and pets. Children must be under adult supervision while using this product. This product contains 80% ethyl alcohol and may damage certain surfaces. Always test in an inconspicuous area first to ensure the surface will not be damaged. Not recommended for varnished, painted, or coated surfaces where other solvents may damage the finish. WHO Recommended Formula.